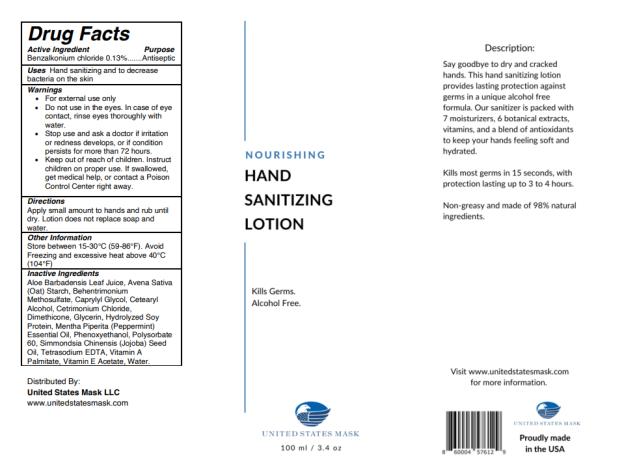 DRUG LABEL: Nourishing Hand Sanitizing
NDC: 82289-1836 | Form: INSERT, EXTENDED RELEASE
Manufacturer: United States Mask LLC
Category: otc | Type: HUMAN OTC DRUG LABEL
Date: 20211001

ACTIVE INGREDIENTS: BENZALKONIUM CHLORIDE 0.13 mg/100 mL
INACTIVE INGREDIENTS: ALOE VERA LEAF; STARCH, OAT; BEHENTRIMONIUM METHOSULFATE; CAPRYLYL GLYCOL; CETOSTEARYL ALCOHOL; CETRIMONIUM CHLORIDE; DIMETHICONE; GLYCERIN; HYDROLYZED SOY PROTEIN (ENZYMATIC; 2000 MW); PEPPERMINT OIL; PHENOXYETHANOL; POLYSORBATE 60; JOJOBA OIL; EDETATE SODIUM; VITAMIN A PALMITATE; .ALPHA.-TOCOPHEROL ACETATE; WATER

Nourishing Hand Sanitizing Lotion

Drug Facts

Purpose

Benzalkonium chloride 0.13%.............................................Antiseptic

Uses

Hand sanitizing and to decrease bacteria on the skin

Warnings

• For external use only

Do not use in the eyes.

• In case of eye contact, rinse eyes thoroughly with water.

Stop use and ask a doctor

• if irritation or redness develops, or if condition persists for more than 72 hours.

Keep out of reach of children.

• Instruct children on proper use. If swallowed, get medical help, or contact a Poison Control Center right away.

Directions

Apply small amount to hands and rub until dry. Lotion does not replace soap and water.

Other Information

Store between 15-30°C (59-86°F). Avoid Freezing and excessive heat above 40°C (104°F)

Inactive Ingredients

Aloe Barbadensis Leaf Juice, Avena Sativa (Oat) Starch, Behentrimonium Methosulfate, Caprylyl Glycol, Cetearyl Alcohol, Cetrimonium Chloride, Dimethicone, Glycerin, Hydrolyzed Soy Protein, Mentha Piperita (Peppermint) Essential Oil, Phenoxyethanol, Polysorbate 60, Simmondsia Chinensis (Jojoba) Seed Oil, Tetrasodium EDTA, Vitamin A Palmitate, Vitamin E Acetate, Water.

PRINCIPAL DISPLAY PANEL

Nourishing
Hand
Sanitizing
Lotion

100 ml/ 3.4 oz